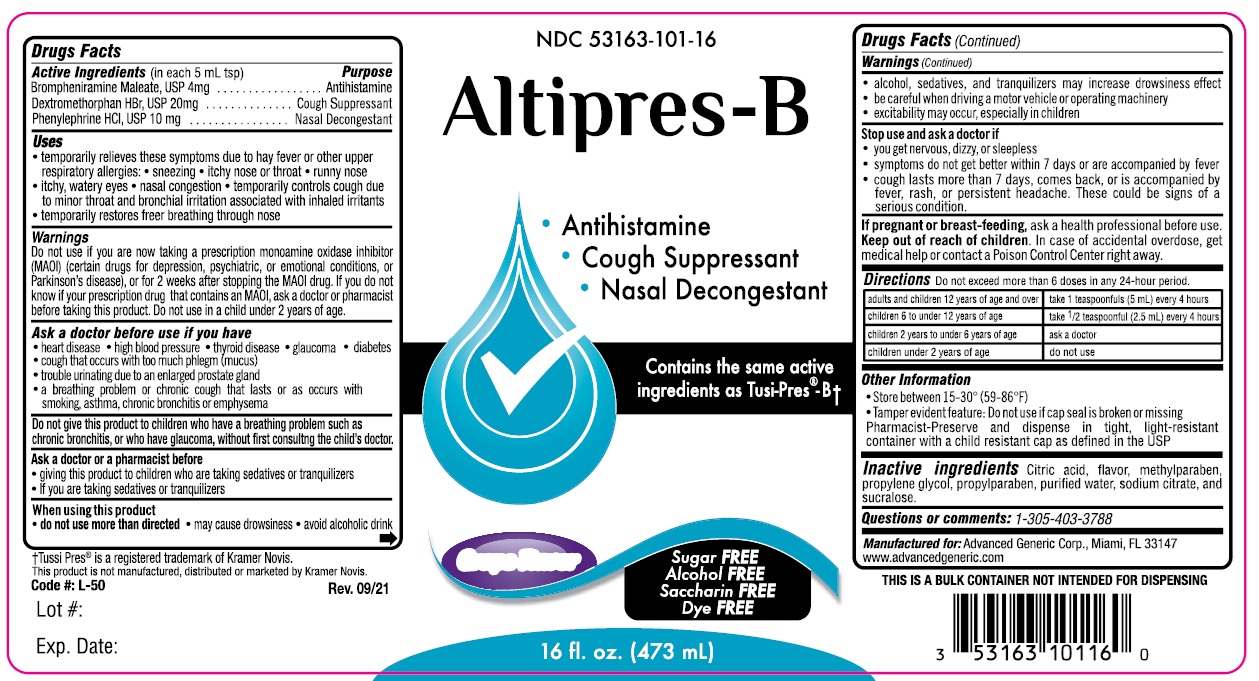 DRUG LABEL: Altipres-B
NDC: 53163-101 | Form: LIQUID
Manufacturer: Alternative Pharmacal Corporation
Category: otc | Type: HUMAN OTC DRUG LABEL
Date: 20251231

ACTIVE INGREDIENTS: DEXTROMETHORPHAN HYDROBROMIDE 20 mg/5 mL; PHENYLEPHRINE HYDROCHLORIDE 10 mg/5 mL; BROMPHENIRAMINE MALEATE 4 mg/5 mL
INACTIVE INGREDIENTS: WATER; CITRIC ACID MONOHYDRATE; METHYLPARABEN; PROPYLENE GLYCOL; PROPYLPARABEN; SODIUM CITRATE; SUCRALOSE

Alt-AltipresB 101

Active Ingredients (in each 5 mL tsp) Purpose

Brompheniramine maleate 4 mg Antihistamine

Dextromethorphan HBr 20 mg Cough Suppressant

Phenylephrine HCl 10 mg Nasal Decongestant

Purpose

Antihistamine

Cough Suppressant

Nasal Decongestant

Uses

- temporarily relieves symptoms due to hay fever or other upper respiratory allergies:
- sneezing
- itchy nose or throat
- runny nose
- itchy, water eyes
- nasal congestion
- temporarily controls cough due to minor throat and bronchial irritation associated with inhaled irritants
- temporarily restores freer breathing through nose

Warnings

Do not use if you are now taking a prescription monoamine oxidase inhibitor (MAOI) (certain drugs for depression, psychiatric, or emotional conditions, or Parkinson's disease), or for 2 weeks after stopping the MAOI drug. If you do not know if your prescription drug contains an MAOI, ask a doctor or pharmacist before taking this product. Do not use on a child under 2 years of age.

Ask a doctor before use if you have

- heart disease
- high blood pressure
- thyroid disease
- glaucoma
- diabetes
- cough that occurs with too much phlegm (mucus)
- trouble urinating due to an enlarged prostate gland
- a breathing problem or chronic cough that lasts or as occurs with smoking, asthma, chronic bronchitis or emphysema

Ask a doctor or a pharmacist before

- giving this product to children who are taking sedatives or tranquilizers
- if you are taking sedatives or tranquilizers

DO NOT USE

Do not give this product to children who have a breathing problem such as chronic bronchitis, or who have glaucoma, without first consulting the child's doctor.

When using this product

- do not use more than directed
- may cause drowsiness
- avoid alcoholic drink
- alcohol, sedatives and tranquilizers may increase drowsiness effect
- be careful when driving a motor vehicle or operating machinery
- excitability may occur, especially in children

Stop use and ask a doctor if

- you get nervous, dizzy or sleeplessness
- symptoms do not get better within 7 days or are accompanied by fever
- cough lasts more than 7 days, comes back or is accompanied by fever, rash or persistent headache. These could be signs of a serious condition.

Keep out of reach of children.In case of accidental overdose, get medical help or contact a Poison Control Center right away.

PREGNANCY OR BREAST FEEDING

If pregnant or breast-feeding,ask a health professional before use.

DOSAGE AND ADMINISTRATION

DirectionsDo not exceed more than 6 doses in any 24-hour period.

adults and children 12 years of age and over | take 1 teaspoonfuls (5 mL) every 4 hours
children 6 to under 12 years of age | take 1/2 teaspoonfuls (2.5mL) every 4 hours
children 2 years to under 6 years of age | ask a doctor
children under 2 years of age | do not use

INACTIVE INGREDIENT

Inactive Ingredients citric acid, flavor, methylparaben, propylene glycol, propylparaben, pruified water, sodium citrate, and sucralose

Questions or comments: 1-305-403-3788

Alternative Pharmacal Corp. Miami Fl 33147

www.alternativepharmacal.com